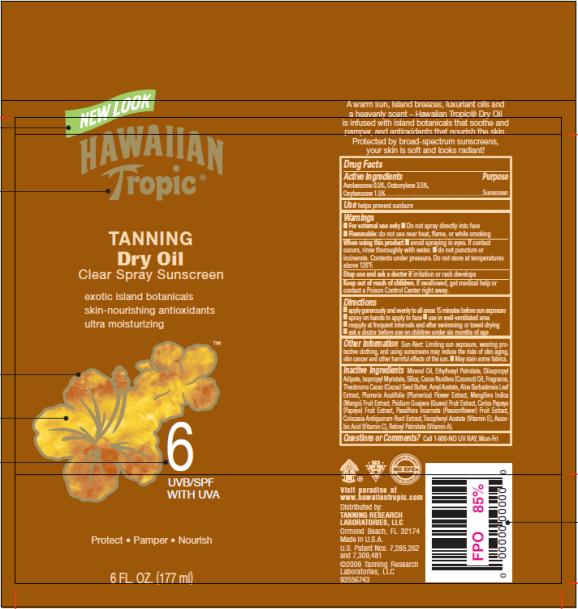 DRUG LABEL: Hawaiian Tropic Tanning Dry SPF 6
NDC: 17630-2013 | Form: OIL
Manufacturer: Accra-Pac, Inc.
Category: otc | Type: HUMAN OTC DRUG LABEL
Date: 20100325

ACTIVE INGREDIENTS: AVOBENZONE 0.005 mL/1 mL; OCTOCRYLENE 0.035 mL/1 mL; OXYBENZONE 0.015 mL/1 mL
INACTIVE INGREDIENTS: MINERAL OIL; ETHYLHEXYL PALMITATE; DIISOPROPYL ADIPATE; ISOPROPYL MYRISTATE; SILICON DIOXIDE; COCONUT OIL; AMYL ACETATE; ALOE VERA LEAF; PLUMERIA EXTRACT; GUAVA; PAPAYA; PASSIFLORA INCARNATA TOP; .ALPHA.-TOCOPHEROL ACETATE, D-; ASCORBIC ACID; VITAMIN A PALMITATE; CHOCOLATE; MANGO

Hawaiian Tropic Tanning Dry Oil SPF 6

Drug Facts

Active Ingredients

Avobenzone 0.005mL / 1mL

Octocrylene 0.035mL / 1mL

Oxybenzone 0.015mL / 1mL

Purpose

Sunscreen

Use

helps prevent sunburn

Warnings

- For external use only
- Do not spray directly into face
- Flammable: do not use near heat, flame, or while smoking

When using this product

- avoid spraying in eyes. If contact occurs, rinse thoroughly with water.
- do not puncture or incinerate. Contents under pressure. Do not store at temperatures above 120°F.

Stop use and ask a doctor if

irritation or rash develops

Keep out of reach of children.

If swallowed, get medical help or contact a Poison Control Center right away.

Directions

- apply generously and evenly to all areas 15 minutes before sun exposure
- spray on hands to apply to face
- use in well-ventilated area
- reapply at frequent intervals and after swimming or towel drying
- ask a doctor before use on children under six months of age

Other Information

Sun Alert: Limiting sun exposure, wearing protective clothing, and using sunscreens may reduce the risks of skin aging, skin cancer and other harmful effects of the sun.

- May stain some fabrics.

Inactive Ingredients

Mineral Oil, Ethylhexyl Palmitate, Diisopropyl Adipate, Isopropyl Myristate, Silica, Cocos Nucifera (Coconut) Oil, Fragrance, Theobroma Cacao (Cocoa) Seed Butter, Amyl Acetate, Aloe Barbadensis Leaf Extract, Plumeria Acutifolia (Plumerica) Flower Extract, Mangifera Indica (Mango) Fruit Extract, Psidium Guajava (Guava) Fruit Extract, Carica Papaya (Papaya) Fruit Extract, Passiflora Incarnata (Passionflower) Fruit Extract, Colocasia Antiquorum Root Extract, Tocopheryl Acetate (Vitamin E), Ascorbic Acid (Vitamin C), Retinyl Palmitate (Vitamin A).

Questions or Comments?

Call 1-800-NO UV RAY, Mon-Fri

Distributed by:
TANNING RESEARCH
LABORATORIES, LLC
Ormond Beach, FL 32174
Made in U.S.A.

PRINCIPAL DISPLAY PANEL

NEW LOOK
HAWAIIAN
Tropic®
TANNING
Dry Oil
Clear Spray Sunscreen
exotic island botanicals
skin-nourishing antioxidants
ultra moisturizing
6
UVB/SPF
WITH UVA
Protect Pamper Nourish
6 FL. OZ. (177 ml)